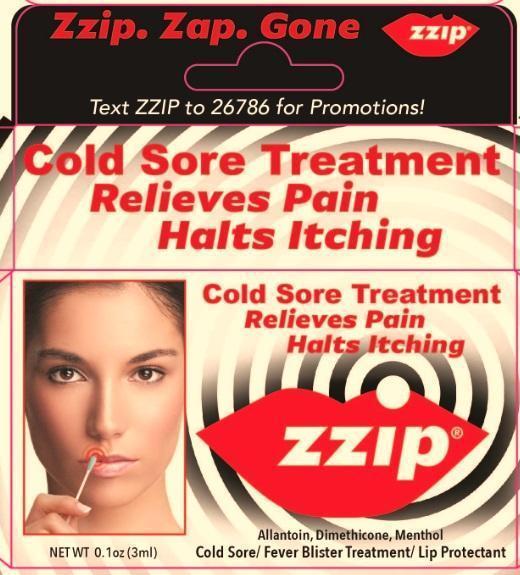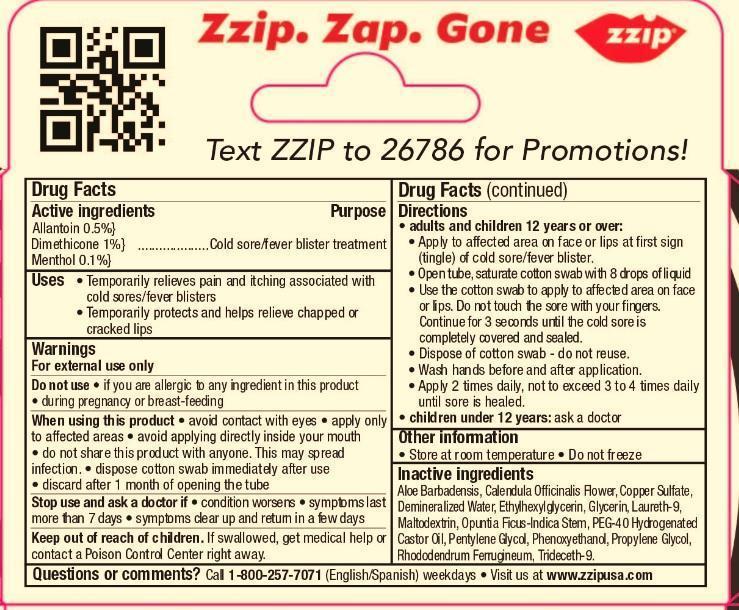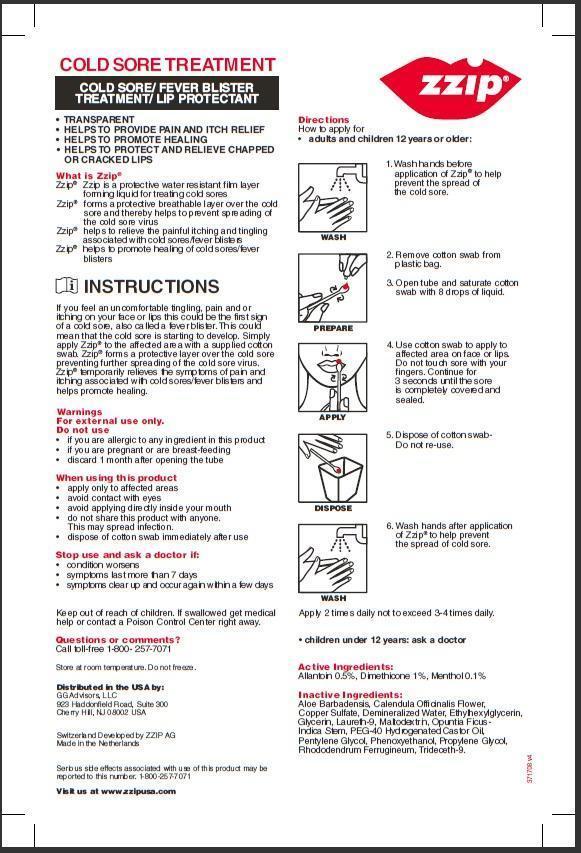 DRUG LABEL: Zzip Cold Sore Treatment
NDC: 70019-100 | Form: SOLUTION
Manufacturer: Zzip AG
Category: otc | Type: HUMAN OTC DRUG LABEL
Date: 20150730

ACTIVE INGREDIENTS: ALLANTOIN 5 mg/1 mL; DIMETHICONE 10 mg/1 mL; MENTHOL 1 mg/1 mL
INACTIVE INGREDIENTS: ALOE; CALENDULA OFFICINALIS FLOWER; BASIC COPPER SULFATE; WATER; ETHYLHEXYLGLYCERIN; GLYCERIN; LAURETH-9; MALTODEXTRIN; OPUNTIA FICUS-INDICA STEM; PEG-40 CASTOR OIL; PENTYLENE GLYCOL; TRIDECETH-9

Zzip Cold Sore Treatment

Drug Facts

Active Ingredients

Allantoin 0.5%

Dimethicone 1%

Menthol 0.1%

Purpose

Cold sore/fever blister treatment

Uses

- Temporarily relieves the pain and itching associated with cold sores/fever blisters.

- Temporarily protects and helps relieve chapped or cracked lips.

Warnings

For external use only

Do not use

- if you are allergic to any ingredient in this product

- during pregnancy or breast-feeding.

When using this product

- avoid contact with eyes

- apply only to affected areas

- avoid applying directy inside your mouth

- do not share this product with anyone. This may spread infection.

- dispose cotton swab immediately after use

- discard after 1 month of opening the tube

Stop use and ask a doctor if

- condition worsens

- symptoms last more than 7 days

- symptoms clear up and return in a few days.

Keep out of reach of children.

If swallowed, get medical help or contact a Poison Control Center right away.

Directions

adults and children 12 years or over:

- Apply to affected area on face or lips at first sign (tingle) of cold sore/fever blister

- Open tube, saturate cotton swab with 8 drops of liquid

- Use the cotton swab to apply to affeted area on face or lips. Do ot touch the sore with your fingers. Continue for 3 seconds until the cold sore is completely covered and sealed.

- Dispose of cotton swab - do not reuse

- Wash hands before and after application.

- Apply 2 times daily, not to exceed 3 to 4 times daily until sore is healed

children under 12 years: ask a doctor

Other information

Store at room temperature

Do not freeze

Inactive Ingredients

Aloe Barbadensis, Calendula Officinalis Flower, Copper Sulfate, Demineralized water, Ethylhexylglycerin, Glycerin, Laureth-9, Maltodextrin, Opuntia Ficus Indica Stem, PEG-40 Hydrogenated CAstor Oil, Pentylene Glycol, Phenoxyethanol, Propylene Glycol, Rhododendrum Ferrugineum, Trideceth-9.

Questions or comments?

Call 1-800-257-7071 (English/Spanish) Weekdays

Visit us at www.zzipusa.com

Distributed in the USA by:

GG Advisors, LLC

923 Haddonfield Rd., Suite 300

Cherry Hill, NJ 08002

1-800-257-7071

Switzerland developed by Zzip AG

Made in the Netherlands